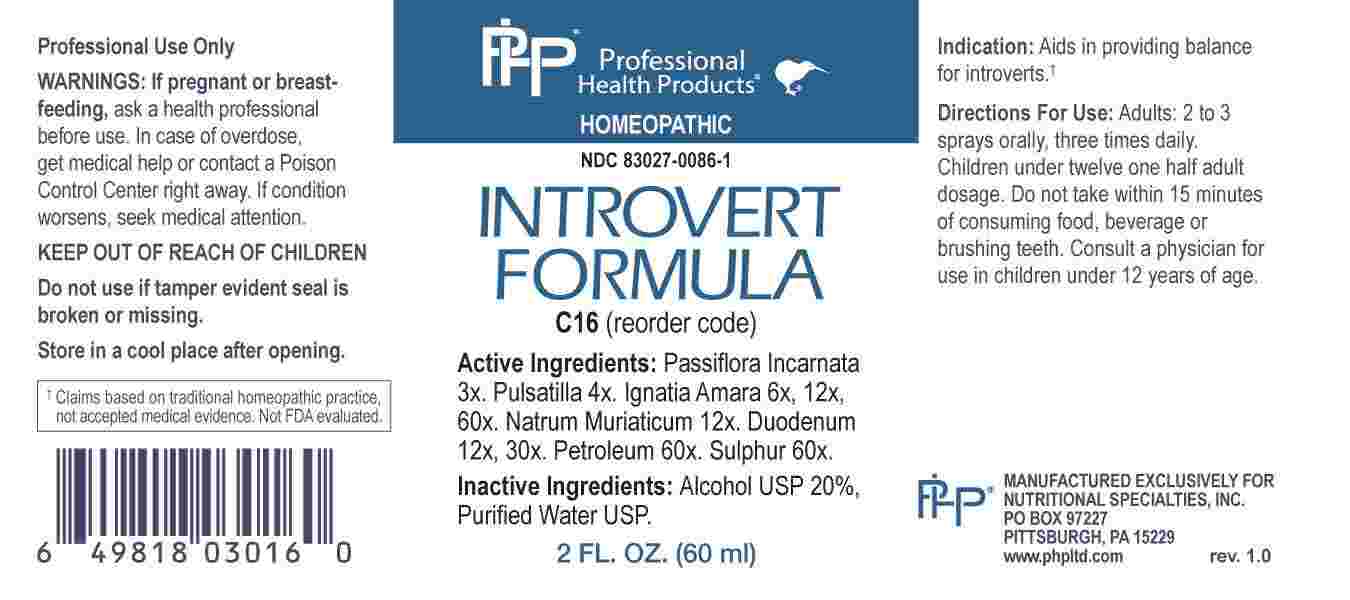 DRUG LABEL: Introvert Formula
NDC: 83027-0086 | Form: SPRAY
Manufacturer: Nutritional Specialties, Inc.
Category: homeopathic | Type: HUMAN OTC DRUG LABEL
Date: 20230711

ACTIVE INGREDIENTS: PASSIFLORA INCARNATA FLOWERING TOP 3 [hp_X]/1 mL; PULSATILLA PRATENSIS WHOLE 4 [hp_X]/1 mL; STRYCHNOS IGNATII SEED 6 [hp_X]/1 mL; SODIUM CHLORIDE 12 [hp_X]/1 mL; SUS SCROFA DUODENUM 12 [hp_X]/1 mL; KEROSENE 60 [hp_X]/1 mL; SULFUR 60 [hp_X]/1 mL
INACTIVE INGREDIENTS: WATER; ALCOHOL

DRUG FACTS:

ACTIVE INGREDIENTS:

Passiflora Incarnata 3X, Pulsatilla 4X, Ignatia Amara 6X, 12X, 60X, Natrum Muriaticum 12X, Duodenum 12X, 30X, Petroleum 60X, Sulphur 60X.

PURPOSE:

Aids in providing balance for introverts.†

†Claims based on traditional homeopathic practice, not accepted medical evidence. Not FDA evaluated.

WARNINGS:

Professional Use Only

If pregnant or breast-feeding, ask a health professional before use.

In case of overdose, get medical help or contact a Poison Control Center right away.

If condition worsens, seek medical attention.

KEEP OUT OF REACH OF CHILDREN

Do not use if tamper evident seal is broken or missing.

Store in a cool place after opening

KEEP OUT OF REACH OF CHILDREN:

In case of overdose, get medical help or contact a Poison Control Center right away.

DIRECTIONS:

Adults: 2 to 3 sprays orally, three times daily. Children under twelve one half adult dosage. Do not take within 15 minutes of consuming food, beverage or brushing teeth. Consult a physician for use in children under 12 years of age.

INDICATIONS:

Aids in providing balance for introverts.†

†Claims based on traditional homeopathic practice, not accepted medical evidence. Not FDA evaluated.

INACTIVE INGREDIENTS:

Alcohol USP 20%, Purified Water USP.

QUESTIONS:

MANUFACTURED EXCLUSIVELY FOR

NUTRITIONAL SPECIALTIES, INC.

PO BOX 97227

PITTSBURG, PA 15229

www.phpltd.com

PACKAGE LABEL DISPLAY:

Professional

Health Products

HOMEOPATHIC

NDC 83027-0086-1

INTROVERT

FORMULA

2 FL. OZ (60 ml)